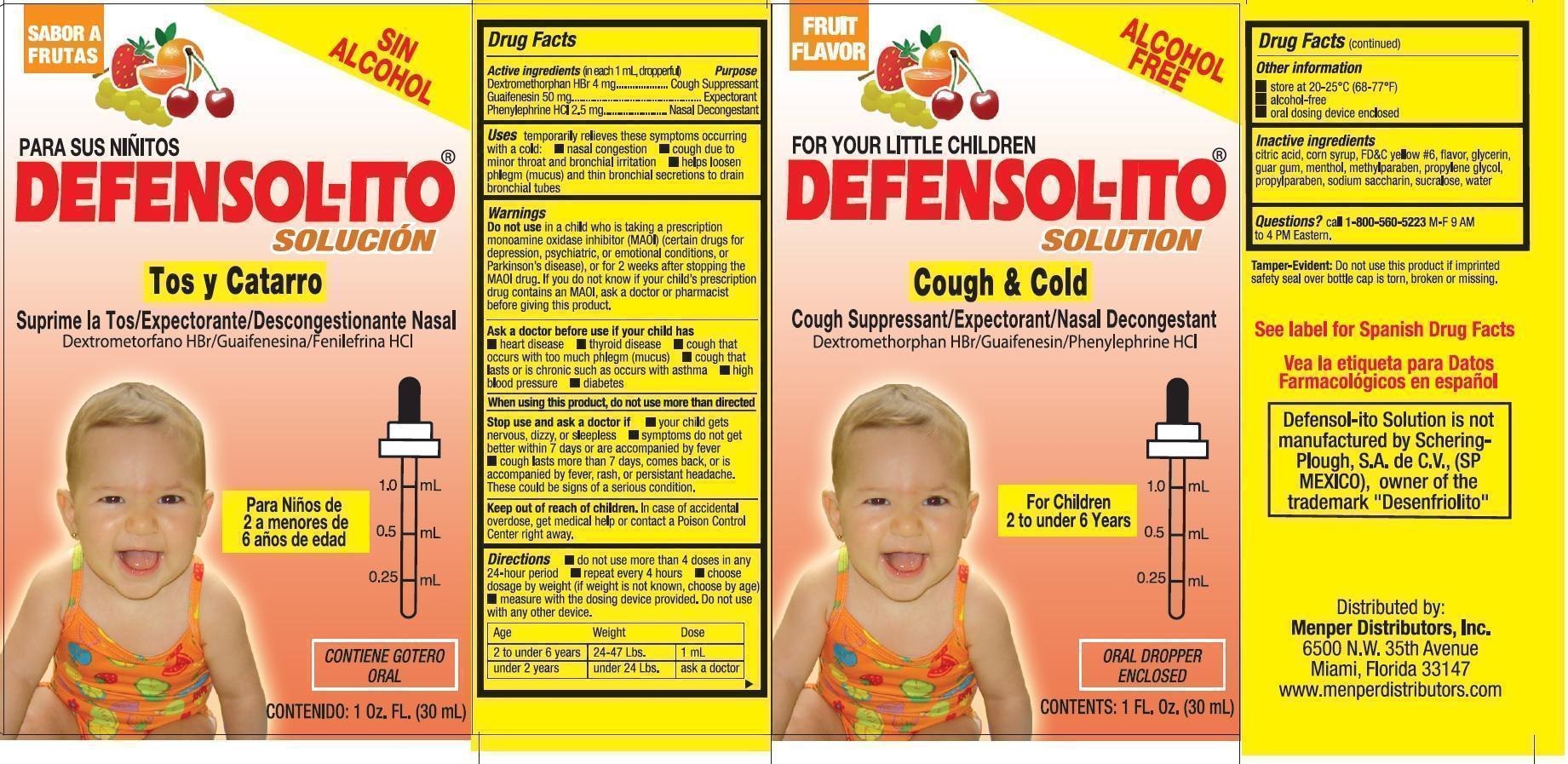 DRUG LABEL: Defensol-ito
NDC: 53145-333 | Form: SOLUTION
Manufacturer: Menper Distributors, Inc
Category: otc | Type: HUMAN OTC DRUG LABEL
Date: 20250722

ACTIVE INGREDIENTS: DEXTROMETHORPHAN HYDROBROMIDE 4 mg/1 mL; GUAIFENESIN 50 mg/1 mL; PHENYLEPHRINE HYDROCHLORIDE 2.5 mg/1 mL
INACTIVE INGREDIENTS: CORN SYRUP; FD&C YELLOW NO. 6; GLYCERIN; GUAR GUM; MENTHOL; METHYLPARABEN; PROPYLENE GLYCOL; PROPYLPARABEN; CITRIC ACID MONOHYDRATE; SACCHARIN SODIUM; SUCRALOSE; WATER

Defensol-ito solution

Active Ingredient (in each 1 mL, dropperful) Purpose

Dextromethorphan 4 mg............................................................................Cough Suppressant

Guiafenesin 50 mg............................................................................Expectorant

Phenylephrine HCl 2.5mg...................................................................Nasal Decongestant

PURPOSE

Cough Suppressant

Expectorant

Nasal Decongestant

INDICATIONS AND USAGE

Uses temporarily relives these symptoms occuring with cold:

- nasal congestion
- cough due to minor throat and bronchial irriatation
- helps loosen phlegm (mucus) and thin bronchial secretions to drain bronchial tubes.

Do not use in child who is taking a prescription monoamine oxidase inhibitor (MAOI) (certain drugs for depression, psychiatric, or emotional conditions, or Parkinson's disease), or for 2 weeks after stopping the MAOI drug. If you do not know if your child's prescription drug contains an MAOI, ask a doctor or pharmacist before giving this product.

Ask a doctor before use if your child has

- heart disease
- thyroid disease
- cough that occurs with too much phlegm (mucus)
- cough that lasts or is chronic such as occurs with asthma
- high blood pressure
- diabetes

When using this product, do not use more than directed

Stop use and ask doctor if

- your child gets nervous, dizzy, or sleepless
- symptoms do not get better within 7 days, comes back, or is accompanied by fever
- cough lasts more than 7 days, comes back, or is accompanied by fever, rash or persistant headache. These could b signs of a serious condition.

KEEP OUT OF REACH OF CHILDREN

Keep ot of reach of children. In case of accidental overdose, get medical help or contact a Poison Control Center right away.

Directions

- do not use more than doses in any 24-hour period
- repeat every 4 hours
- choose dosage by weight (if weight is not known, choose by age)
- measure with the dosing device provided. Do not use with any other device.

Age Weight Dose

2 to under 6 years 24-47 Lbs 1 mL

under 2 years under 24 Lbs ask as doctor

QUESTIONS

Questions? call 1-800-560-5223 M-F 9 AM to 4 PM Eastern

Inactive ingradients

citric acid, corn syrup, FD&C yellow #6, flavor, glycerin, guar gum,menthol, methylparaben, propylene glycol, propylparaben, sodium saccharin, sucralose, water